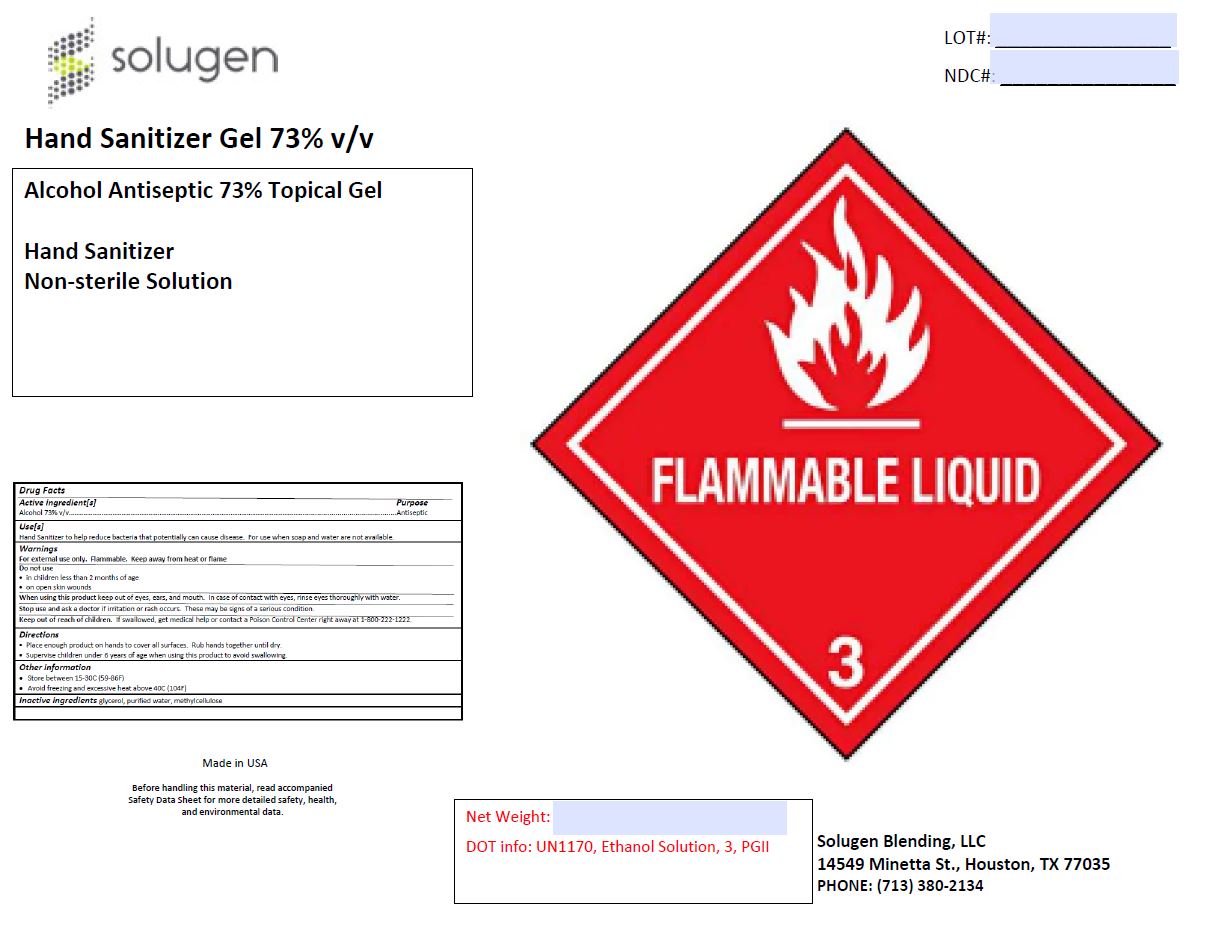 DRUG LABEL: Hand Sanitizer Gel 73% Alcohol Antiseptic
NDC: 79975-008 | Form: GEL
Manufacturer: Solugen Blending LLC
Category: otc | Type: HUMAN OTC DRUG LABEL
Date: 20200911

ACTIVE INGREDIENTS: ALCOHOL 73 mL/100 mL
INACTIVE INGREDIENTS: HYDROXYMETHYL CELLULOSE 1 mL/100 mL; GLYCERIN 1.15 mL/100 mL; WATER

Hand Sanitizer Gel 73% Alcohol Antiseptic

Hand Sanitizer Gel 73% Alcohol Antiseptic

This is a hand sanitizer manufactured according to the part333A of the OTC monograph.

The hand sanitizer is manufactured using only the following United States Pharmacopoeia (USP) grade ingredients in the preparation of the product (percentage formulation)

a. Alcohol (ethanol) (USP or Food Chemical Codex (FCC) grade) (73%, volume/volume (v/v) in an aqueos solution denatured according to Alcohol and Tobacco Bureau regulations in 27 CFR part 20.

b. Glycerol (1.15% v/v).

c. Hydroxymethyl Cellulose (1.00% v/v).

d. Sterile distilled water or boiled cold water.

Active Ingredient(s)

Alcohol 73% v/v. Purpose: Antiseptic

Purpose

Antiseptic, Hand Sanitizer

Use

Hand Sanitizer to help reduce bacteria that potentially can cause disease. For use when soap and water are not available.

Warnings

For external use only. Flammable. Keep away from heat or flame

Do not use

- in children less than 2 months of age
- on open skin wounds

When using this product keep out of eyes, ears, and mouth. In case of contact with eyes, rinse eyes thoroughly with water.
Stop use and ask a doctor if irritation or rash occurs. These may be signs of a serious condition.
Keep out of reach of children. If swallowed, get medical help or contact a Poison Control Center right away.

Stop use and ask a doctor if irritation or rash occurs. These may be signs of a serious condition.

Keep out of reach of children. If swallowed, get medical help or contact a Poison Control Center right away.

Directions

- Place enough product on hands to cover all surfaces. Rub hands together until dry.
- Supervise children under 6 years of age when using this product to avoid swallowing.

Other information

- Store between 15-30C (59-86F)
- Avoid freezing and excessive heat above 40C (104F)

Inactive ingredients

glycerin, methyl cellulose, purified water USP

Hand Sanitizer Gel 73% Alcohol Antiseptic

18927000 mL NDC: 79975-008-01